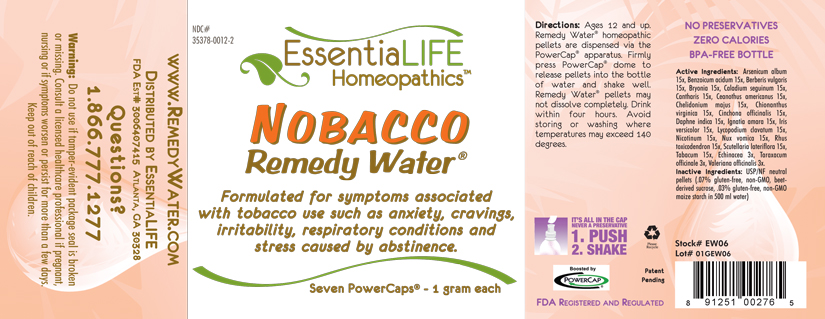 DRUG LABEL: Nobacco Remedy Water 
NDC: 35378-0012 | Form: PELLET
Manufacturer: Georgetown Health, LLC DBA EssentiaLife
Category: homeopathic | Type: HUMAN OTC DRUG LABEL
Date: 20120610

ACTIVE INGREDIENTS: Arsenic Trioxide 15 [hp_X]/1 mg; Benzoic Acid 15 [hp_X]/1 mg; Berberis Vulgaris Root Bark 15 [hp_X]/1 mg; Bryonia Alba Root 15 [hp_X]/1 mg; Dieffenbachia Seguine 15 [hp_X]/1 mg; Lytta Vesicatoria 15 [hp_X]/1 mg; Ceanothus Americanus Leaf 15 [hp_X]/1 mg; Chelidonium Majus 15 [hp_X]/1 mg; Chionanthus Virginicus Bark 15 [hp_X]/1 mg; Cinchona Officinalis Bark 15 [hp_X]/1 mg; Daphne Odora Bark 15 [hp_X]/1 mg; Strychnos Ignatii Seed 15 [hp_X]/1 mg; Lycopodium Clavatum Spore 15 [hp_X]/1 mg; Nicotine 15 [hp_X]/1 mg; Strychnos Nux-vomica Seed 15 [hp_X]/1 mg; Toxicodendron Pubescens Leaf 15 [hp_X]/1 mg; Scutellaria Lateriflora 15 [hp_X]/1 mg; Tobacco Leaf 15 [hp_X]/1 mg; Echinacea, Unspecified 3 [hp_X]/1 mg; Taraxacum Officinale 3 [hp_X]/1 mg; Valerian 3 [hp_X]/1 mg; Iris Versicolor Root 15 [hp_X]/1 mg
INACTIVE INGREDIENTS: Starch, Corn; Sucrose

Nobacco Remedy Water®

Active Ingredients

Arsenicum album | 15x
Benzoicum acidum | 15x
Berberis vulgaris | 15x
Bryonia | 15x
Caladium seguinum | 15x
Cantharis | 15x
Ceanothus americanus | 15x
Chelidonium majus | 15x
Chionanthus virginica | 15x
Cinchona officinalis | 15x
Daphne indica | 15x
Ignatia amara | 15x
Iris versicolor | 15x
Lycopodium clavatum | 15x
Nicotinum | 15x
Nux vomica | 15x
Rhus toxicodendron | 15x
Scutellaria lateriflora | 15x
Tabacum | 15x
Echinacea | 3x
Taraxacum officinale | 3x
Valeriana officinalis | 3x

Purpose

Formulated for symptoms associated with tobacco use such as anxiety, cravings, irritability, respiratory conditions and stress caused by abstinence.

Uses

Formulated for symptoms associated with tobacco use such as anxiety, cravings, irritability, respiratory conditions and stress caused by abstinence.

Warnings

Do not use if tamper-evident package seal is broken or missing. Consult a licensed healthcare professional if pregnant, nursing or if symptoms worsen or persist for more than a few days. Keep out of reach of children.

Directions

Ages 12 and up. Remedy Water® homepathic pellets are dispersed via the PowerCap® apparatus. Firmly press PowerCap® dome to release pellets into the bottle of water and shake well. Remedy Water® pellets may not dissolve completely. Drink within four hours. Avoid storing or washing where temperatures may exceed 140 degrees.

Inactive Ingredients

USP/NF neutral pellets (.07% gluten-free, non-GMO, beet-derived sucrose, .03% gluten-free, non-GMO maize starch in 500 ml water)

Other Information

Avoid storing in areas where temperatures may exceed 140 degrees.

Questions?

1.866.777.1277
www.EssentiaLife.com

PRINCIPAL DISPLAY PANEL

NDC# 35378-0012-2

EssentiaLIFE Homeopathics™

Nobacco Remedy Water®

Formulated for symptoms associated with tobacco use such as anxiety, cravings, irritability, respiratory conditions and stress caused by abstinence.

Seven PowerCaps® - 1 gram each

Directions:Ages 12 and up. Remedy Water® homepathic pellets are dispersed via the PowerCap® apparatus. Firmly press PowerCap® dome to release pellets into the bottle of water and shake well. Remedy Water® pellets may not dissolve completely. Drink within four hours. Avoid storing or washing where temperatures may exceed 140 degrees.

IT'S ALL IN THE CAP
NEVER A PRESERVATIVE
1. PUSH
2. SHAKE

Please Recyle

Patent Pending

Boosted by PowerCap®

FDA Registered and Regulated

NO PRESERVATIVES
ZERO CALORIES
BPA-FREE BOTTLE

Active Ingredients: Arsenicum album 15x, Benzoicum acidum 15x, Berberis vulgaris 15x, Bryonia 15x, Caladium seguinum 15x, Cantharis 15x, Ceanothus americanus 15x, Chelidonium majus 15x, Chionanthus virginica 15x, Cinchona officinalis 15x, Daphne indica 15x, Ignatia amara 15x, Iris versicolor 15x, Lycopodium clavatum 15x, Nicotinum 15x, Nux vomica 15x, Rhus toxicodendron 15x, Scutellaria lateriflora 15x, Tabacum 15x, Echinacea 3x, Taraxacum officinale 3x, Valeriana officinalis 3x.

Inactive ingredients: USP/NF neutral pellets (.07% gluten-free, non-GMO, beet-derived sucrose, .03% gluten-free, non-GMO maize starch in 500 ml water)

Stock# EW06

Lot# 01GEW06

www.RemedyWater.com

Distributed by EssentiaLIFE

FDA Est# 3006407415 Atlanta, GA 30328

Questions?

1.866.777.1277

Warning: Do not use if tamper-evident package seal is broken or missing. Consult a licensed healthcare professional if pregnant, nursing or if symptoms worsen or persist for more than a few days. Keep out of reach of children.